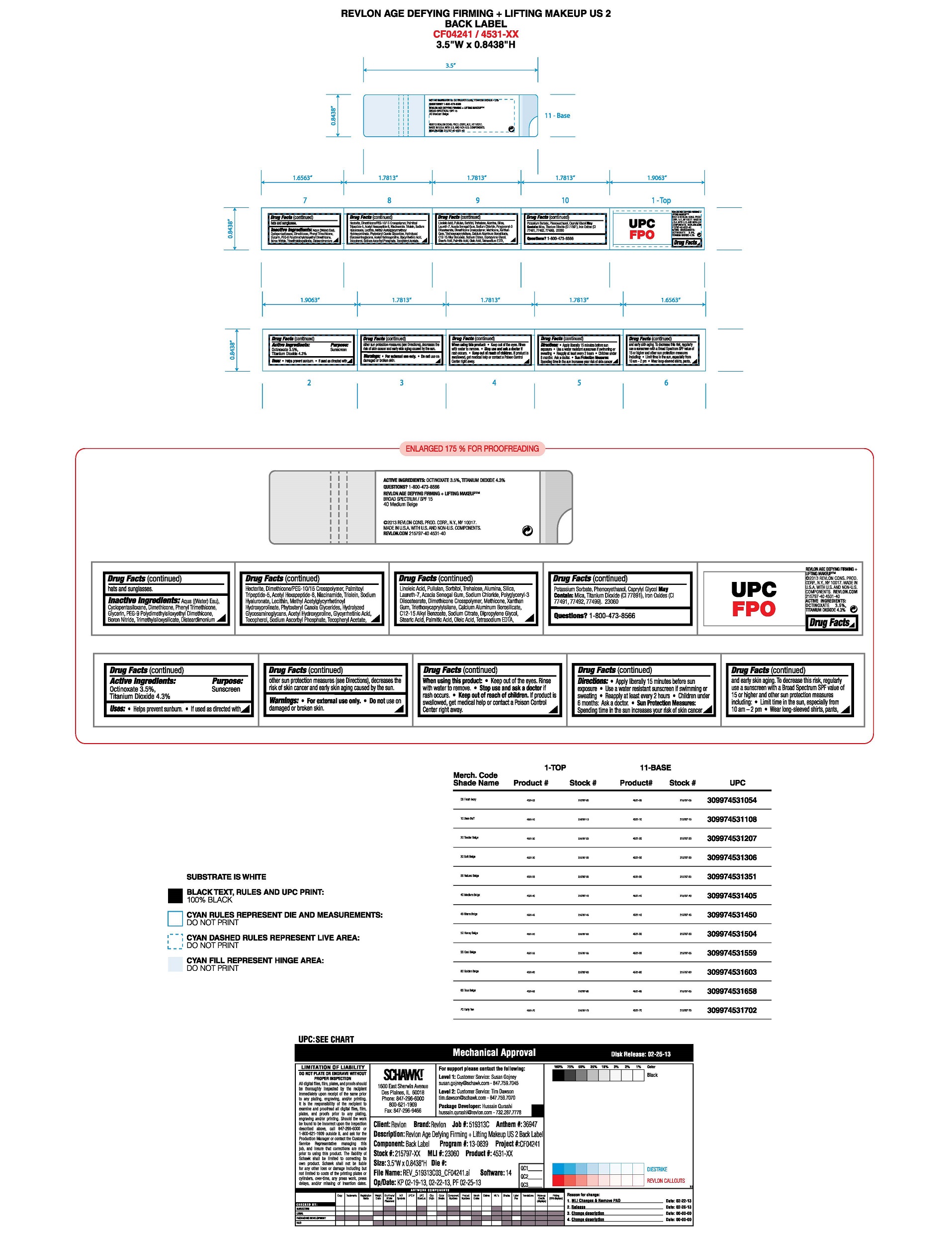 DRUG LABEL: REVLON AGE DEFYING FIRMING  LIFTING MAKEUP SPF 15
NDC: 10967-621 | Form: LIQUID
Manufacturer: Revlon Consumer Products Corp
Category: otc | Type: HUMAN OTC DRUG LABEL
Date: 20241231

ACTIVE INGREDIENTS: OCTINOXATE 3.5 mg/1 mL; TITANIUM DIOXIDE 4.3 mg/1 mL
INACTIVE INGREDIENTS: WATER; DIMETHICONE; PHENYL TRIMETHICONE; METHICONE (20 CST); LAURETH-7; ALUMINUM OXIDE; .ALPHA.-TOCOPHEROL ACETATE; XANTHAN GUM; NIACINAMIDE; TRIMETHYLSILOXYSILICATE (M/Q 0.8-1.0); CYCLOMETHICONE 5; PEG-9 POLYDIMETHYLSILOXYETHYL DIMETHICONE; BORON NITRIDE; DISTEARDIMONIUM HECTORITE; PHENOXYETHANOL; SODIUM CHLORIDE; POTASSIUM SORBATE; TRIETHOXYCAPRYLYLSILANE; SODIUM ASCORBYL PHOSPHATE; TOCOPHEROL; LINOLEIC ACID; LECITHIN, SOYBEAN; PALMITIC ACID; OLEIC ACID; STEARIC ACID; SILICON DIOXIDE; EDETATE SODIUM; ALKYL (C12-15) BENZOATE; GLYCERIN; CAPRYLYL GLYCOL; POLYGLYCERYL-3 DIISOSTEARATE; PULLULAN; SORBITOL; TREHALOSE; CALCIUM ALUMINUM BOROSILICATE; ENOXOLONE; OXACEPROL; ACACIA; DIPROPYLENE GLYCOL; HYALURONATE SODIUM; HYDROLYZED GLYCOSAMINOGLYCANS (BOVINE; 50000 MW); PALMITOYL TRIPEPTIDE-5; ACETYL HEXAPEPTIDE-8

REVLON AGE DEFYING 3X Foundation

Active Ingredients:

Octinoxate: 3.5%

Titanium Dioxide 4.3%

Purpose

Sunscreen

Uses:

•Helps prevent sunburn
•If used as directed with other sun protection measures (see Directions), decreases the risk of skin cancer and early skin aging caused by the sun

Warnings:

•For external use only
•Do notuse on damaged or broken skin
•When using this product: Keep out of eyes. Rinse with water to remove.
•Stop use and ask a doctor if a rash occurs
•Keep out of reach of children. If product is swallowed, get medical help or contact a Poison Control center right away

Directions

•Apply liberally 15 minutes before sun exposure
•Use a water resistant sunscreen if swimming or sweating
•Reapply at least every 2 hours
•Children under 6 months: Ask a doctor.

Sun Protection Measures

Spending time in the sun increases your risk of skin cancer and early skin aging. To decrease this risk, regularly use a sunscreen with a Broad Spectrum SPF value of 15 or higher and other sun protection measures including:
•Limit time in the sun, especially from 10 am - 2 pm
•Wear long-sleeved shirts, pants, hats and sunglasses.

Inactive Ingredients

AQUA ((WATER) EAU), CYCLOPENTASILOXANE, DIMETHICONE, PHENYL TRIMETHICONE, GLYCERIN, PEG-9 POLYDIMETHYLSILOXYETHYL DIMETHICONE, BORON NITRIDE, TRIMETHYLSILOXYSILICATE, DISTEARDIMONIUM HECTORITE, DIMETHICONE/PEG-10/15 CROSSPOLYMER, ALUMINA, CAPRYLYL GLYCOL, PHENOXYETHANOL, SILICA, NIACINAMIDE, LAURETH-7, SODIUM CHLORIDE, POLYGLYCERYL-3 DIISOSTEARATE, PULLULAN, DIMETHICONE CROSSPOLYMER, METHICONE, XANTHAN GUM, POTASSIUM SORBATE, TRIETHOXYCAPRYLYLSILANE, SORBITOL, TREHALOSE, SODIUM ASCORBYL PHOSPHATE, TOCOPHERYL ACETATE, CALCIUM ALUMINUM BOROSILICATE, C12-15 ALKYL BENZOATE, TETRASODIUM EDTA, GLYCYRRHETINIC ACID, ACETYL HYDROXYPROLINE, ACACIA SENEGAL GUM, TOCOPHEROL, SODIUM CITRATE, DIPROPYLENE GLYCOL, METHYL ACETYLGLYCYRRHETINOYL HYDROXYPROLINATE, LINOLEIC ACID, LECITHIN, SODIUM HYALURONATE, PHYTOSTERYL CANOLA GLYCERIDES, HYDROLYZED GLYCOSAMINOGLYCANS, PALMITIC ACID, OLEIC ACID, TRIOLEIN, STEARIC ACID, PALMITOYL TRIPEPTIDE-5, ACETYL HEXAPEPTIDE-8

DOSAGE AND ADMINISTRATION

Apply liberally 15 minutes before sun exposure.

KEEP OUT OF REACH OF CHILDREN

Keep out of the reach of children. If product is swallowed, get medical help or contact a Poison Control Center right away.

Principal Display Panel

REVLON

Age Defying Firming + Lifting Makeup

Broad Spectrum

SPF 15

1.0 fL. OZ/30 mL